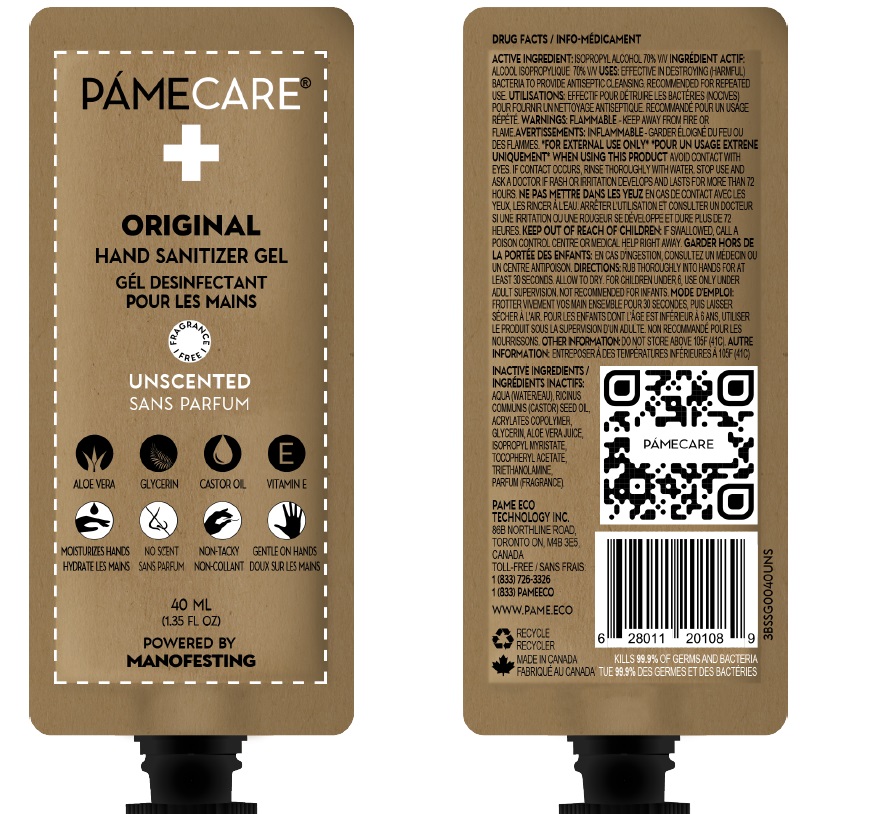 DRUG LABEL: Hand Sanitizer
NDC: 81451-007 | Form: GEL
Manufacturer: Pame Eco Tech
Category: otc | Type: HUMAN OTC DRUG LABEL
Date: 20210125

ACTIVE INGREDIENTS: ISOPROPYL ALCOHOL 70 mL/100 mL
INACTIVE INGREDIENTS: WATER; CASTOR OIL; GLYCERIN; BUTYL ACRYLATE/METHYL METHACRYLATE/METHACRYLIC ACID COPOLYMER (18000 MW); ALOE VERA LEAF; ISOPROPYL MYRISTATE; .ALPHA.-TOCOPHEROL ACETATE; TROLAMINE

Pame Care Original: Unscented Sans Parfum: Hand Sanitizer Gel

ACTIVE INGREDIENT

Isopropyl Alcohol 70% v/v. Purpose: Antiseptic

USES:

Effective indestroying(harmful) bacteria to provide antseptic cleansing recommeded for repeated use .

WARNINGS

For external use only. Flammable . Keep away from fire or flame

DO NOT USE

On children less than 2 months of age

On open skin wounds

Stop use and ask a doctor if irritation or rash develops and lasts for more than 72 hours.

WHEN USING

- Avoid contact with eyes
- If contact occure
- Rinse thoroughly with water.

STORAGE AND HANDLING

Do not store above 105F(41 C)

Keep out of reach of children.If swallowed, get medical help or contact a Poison Control Center right away

INACTIVE INGREDIENT

Water, Ricinus Communis Seed oil, Acrylates copolymer, Glycerin,Aloe Vera Juice, Isopropyl Myristate, Tococpheryl Acetate,Triethanolamine

Parfum

DOSAGE AND ADMINISTRATION

- Rub thoroughly into hands for at least 30 seconds.
- Allow to dry
- For children under 6, use only under adult supervision.
- Not recommended for infants.

PURPOSE

Antiseptic , Hand Sanitizer